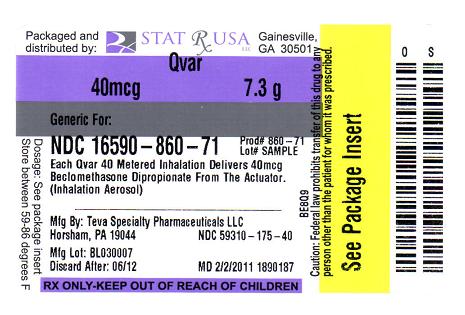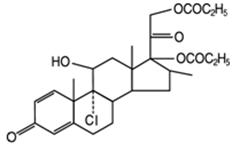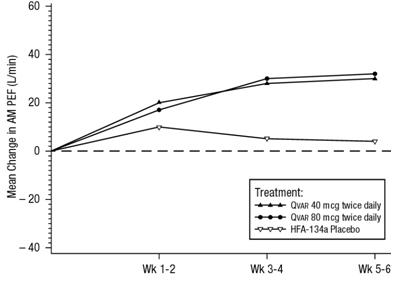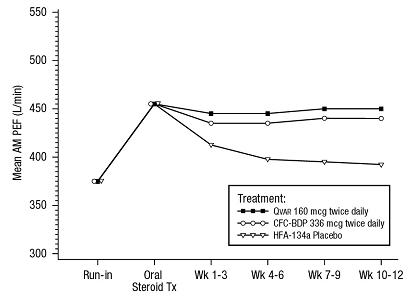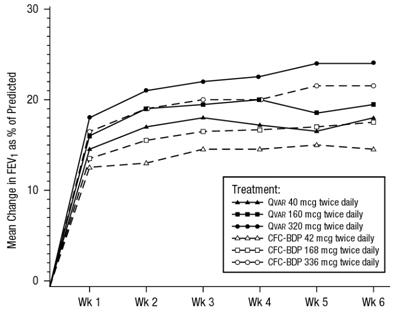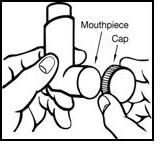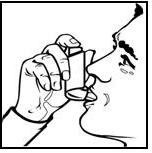 DRUG LABEL: QVAR
NDC: 16590-860 | Form: AEROSOL, METERED
Manufacturer: STAT RX USA LLC
Category: prescription | Type: HUMAN PRESCRIPTION DRUG LABEL
Date: 20110804

ACTIVE INGREDIENTS: BECLOMETHASONE DIPROPIONATE 40 ug/1 1
INACTIVE INGREDIENTS: NORFLURANE; ALCOHOL

DESCRIPTION

The active component of QVAR 40 mcg Inhalation Aerosol and QVAR 80 mcg Inhalation Aerosol is beclomethasone dipropionate, USP, an anti-inflammatory corticosteroid having the chemical name 9-chloro-11β,17,21-trihydroxy-16β-methylpregna-1,4-diene-3,20-dione 17,21-dipropionate. Beclomethasone dipropionate (BDP) is a diester of beclomethasone, a synthetic corticosteroid chemically related to dexamethasone. Beclomethasone differs from dexamethasone in having a chlorine at the 9-alpha carbon in place of a fluorine, and in having a 16 beta-methyl group instead of a 16 alpha-methyl group. Beclomethasone dipropionate is a white to creamy white, odorless powder with a molecular formula of C28H37ClO7 and a molecular weight of 521.1. Its chemical structure is:

QVAR is a pressurized, metered-dose aerosol intended for oral inhalation only. Each unit contains a solution of beclomethasone dipropionate in propellant HFA-134a (1,1,1,2 tetrafluoroethane) and ethanol. QVAR 40 mcg delivers 40 mcg of beclomethasone dipropionate from the actuator and 50 mcg from the valve. QVAR 80 mcg delivers 80 mcg of beclomethasone dipropionate from the actuator and 100 mcg from the valve. Both products deliver 50 microliters (59 milligrams) of solution formulation from the valve with each actuation. The 40 mcg and the 80 mcg canisters provide either 100 inhalations or 120 inhalations. QVAR should be "primed" or actuated twice prior to taking the first dose from a new canister, or when the inhaler has not been used for more than ten days. Avoid spraying in the eyes or face while priming QVAR. This product does not contain chlorofluorocarbons (CFCs).

CLINICAL PHARMACOLOGY

Airway inflammation is known to be an important component in the pathogenesis of asthma. Inflammation occurs in both large and small airways. Corticosteroids have multiple anti-inflammatory effects, inhibiting both inflammatory cells (e.g., mast cells, eosinophils, basophils, lymphocytes, macrophages, and neutrophils) and release of inflammatory mediators (e.g., histamine, eicosanoids, leukotrienes, and cytokines). These anti-inflammatory actions of corticosteroids such as beclomethasone dipropionate contribute to their efficacy in asthma.

Beclomethasone dipropionate is a prodrug that is rapidly activated by hydrolysis to the active monoester, 17 monopropionate (17-BMP). Beclomethasone 17 monopropionate has been shown in vitro to exhibit a binding affinity for the human glucocorticoid receptor which is approximately 13 times that of dexamethasone, 6 times that of triamcinolone acetonide, 1.5 times that of budesonide and 25 times that of beclomethasone dipropionate. The clinical significance of these findings is unknown.

Studies in patients with asthma have shown a favorable ratio between topical anti-inflammatory activity and systemic corticosteroid effects with recommended doses of QVAR.

Pharmacokinetics

Beclomethasone dipropionate (BDP) undergoes rapid and extensive conversion to beclomethasone-17-monopropionate (17-BMP) during absorption. The pharmacokinetics of 17-BMP has been studied in asthmatics given single doses.

Absorption

The mean peak plasma concentration (Cmax) of BDP was 88 pg/ml at 0.5 hour after inhalation of 320 mcg using QVAR (four actuations of the 80 mcg/actuation strength). The mean peak plasma concentration of the major and most active metabolite, 17-BMP, was 1419 pg/ml at 0.7 hour after inhalation of 320 mcg of QVAR. When the same nominal dose is provided by the two QVAR strengths (40 and 80 mcg/actuation), equivalent systemic pharmacokinetics can be expected. The Cmax of 17-BMP increased dose proportionally in the dose range of 80 and 320 mcg.

Metabolism

Three major metabolites are formed via cytochrome P450 3A catalyzed biotransformation - beclomethasone-17-monopropionate (17-BMP), beclomethasone-21-monopropionate (21-BMP) and beclomethasone (BOH). Lung slices metabolize BDP rapidly to 17-BMP and more slowly to BOH. 17-BMP is the most active metabolite.

Distribution

The in vitro protein binding for 17-BMP was reported to be 94-96% over the concentration range of 1000 to 5000 pg/mL. Protein binding was constant over the concentration range evaluated. There is no evidence of tissue storage of BDP or its metabolites.

Elimination

The major route of elimination of inhaled BDP appears to be via hydrolysis. More than 90% of inhaled BDP is found as 17-BMP in the systemic circulation. The mean elimination half-life of 17-BMP is 2.8 hours. Irrespective of the route of administration (injection, oral or inhalation), BDP and its metabolites are mainly excreted in the feces. Less than 10% of the drug and its metabolites are excreted in the urine.

Special Populations

Formal pharmacokinetic studies using QVAR were not conducted in any special populations.

Pediatrics

The pharmacokinetics of 17-BMP, including dose and strength proportionalities, is similar in children and adults, although the exposure is highly variable. In 17 children (mean age 10 years), the Cmax of 17-BMP was 787 pg/ml at 0.6 hour after inhalation of 160 mcg (four actuations of the 40 mcg/actuation strength of HFA beclomethasone dipropionate). The systemic exposure to 17-BMP from 160 mcg of HFA-BDP administered without a spacer was comparable to the systemic exposure to 17-BMP from 336 mcg CFC-BDP administered with a large volume spacer in 14 children (mean age 12 years). This implies that approximately twice the systemic exposure to 17-BMP would be expected for comparable mg doses of HFA-BDP without a spacer and CFC-BDP with a large volume spacer.

Pharmacodynamics

Improvement in asthma control following inhalation can occur within 24 hours of beginning treatment in some patients, although maximum benefit may not be achieved for 1 to 2 weeks, or longer. The effects of QVAR on the hypothalamic-pituitary-adrenal (HPA) axis were studied in 40 corticosteroid naive patients. QVAR, at doses of 80, 160 or 320 mcg twice daily was compared with placebo and 336 mcg twice daily of beclomethasone dipropionate in a CFC propellant based formulation (CFC-BDP). Active treatment groups showed an expected dose-related reduction in 24-hour urinary free cortisol (a sensitive marker of adrenal production of cortisol). Patients treated with the highest recommended dose of QVAR (320 mcg twice daily) had a 37.3% reduction in 24-hour urinary free cortisol compared to a reduction of 47.3% produced by treatment with 336 mcg twice daily of CFC-BDP. There was a 12.2% reduction in 24 hour urinary free cortisol seen in the group of patients that received 80 mcg twice daily of QVAR and a 24.6% reduction in the group of patients that received 160 mcg twice daily. An open label study of 354 asthma patients given QVAR at recommended doses for one year assessed the effect of QVAR treatment on the HPA axis (as measured by both morning and stimulated plasma cortisol). Less than 1% of patients treated for one year with QVAR had an abnormal response (peak less than 18 mcg/dL) to short-cosyntropin test.

CLINICAL TRIALS

Blinded, randomized, parallel, placebo-controlled and active-controlled clinical studies were conducted in 940 adult asthma patients to assess the efficacy and safety of QVAR in the treatment of asthma. Fixed doses ranging from 40 mcg to 160 mcg twice daily were compared to placebo, and doses ranging from 40 mcg to 320 mcg twice daily were compared with doses of 42 mcg to 336 mcg twice daily of an active CFC-BDP comparator. These studies provided information about appropriate dosing through a range of asthma severity. A blinded, randomized, parallel, placebo-controlled study was conducted in 353 pediatric patients (age 5-12 years) to assess the efficacy and safety of HFA beclomethasone dipropionate in the treatment of asthma. Fixed doses of 40 mcg and 80 mcg twice daily were compared with placebo in this study. In these adult and pediatric efficacy trials, at the doses studied, measures of pulmonary function [forced expiratory volume in 1 second (FEV1) and morning peak expiratory flow (AM PEF)] and asthma symptoms were significantly improved with QVAR treatment when compared to placebo.

In controlled clinical trials with adult patients not adequately controlled with beta-agonist alone, QVAR was effective at improving asthma control at doses as low as 40 mcg twice daily (80 mcg/day). Comparable asthma control was achieved at lower daily doses of QVAR than with CFC-BDP. Treatment with increasing doses of both QVAR and CFC-BDP generally resulted in increased improvement in FEV1. In this trial the improvement in FEV1 across doses was greater for QVAR than for CFC-BDP, indicating a shift in the dose response curve for QVAR.

Patients Not Previously Receiving Corticosteroid Therapy

In a 6 week clinical trial, 270 steroid naive patients with symptomatic asthma being treated with as-needed beta-agonist bronchodilators, were randomized to receive either 40 mcg twice daily of QVAR, 80 mcg twice daily of QVAR, or placebo. Both doses of QVAR were effective in improving asthma control with significantly greater improvements in FEV1, AM PEF, and asthma symptoms than with placebo. Shown below is the change from baseline in AM PEF during this trial.

A 6-Week Clinical Trial in Patients with Mild to Moderate Asthma Not on
Corticosteroid Therapy Prior to Study Entry:
Mean Change in AM PEF

In a 6-week clinical trial, 256 patients with symptomatic asthma being treated with as-needed beta-agonist bronchodilators, were randomized to receive either 160 mcg twice daily of QVAR (delivered as either 40 mcg/actuation or 80 mcg/actuation) or placebo. Treatment with QVAR significantly improved asthma control, as assessed by FEV1, AM PEF, and asthma symptoms, when compared to treatment with placebo. Comparable improvement in AM PEF was seen for patients receiving 160 mcg twice daily QVAR from the 40 mcg and 80 mcg strength products.

Patients Responsive to a Short Course of Oral Corticosteroids

In another clinical trial, 347 patients with symptomatic asthma, being treated with as-needed inhaled beta-agonist bronchodilators and, in some cases, inhaled corticosteroids, were given a 7-12 day course of oral corticosteroids and then randomized to receive either 320 mcg daily of QVAR, 672 mcg of CFC-BDP, or placebo. Patients treated with either QVAR or CFC-BDP had significantly better asthma control, as assessed by AM PEF, FEV1 and asthma symptoms, and fewer study withdrawals due to asthma symptoms, than those treated with placebo over 12 weeks of treatment. A daily dose of 320 mcg QVAR administered in divided doses provided comparable control of AM PEF and FEV1 as 672 mcg of CFC-BDP. Shown below are the mean AM PEF results from this trial.

A 12-Week Clinical Trial in Moderate Symptomatic Patients with
Asthma Responding to Oral Corticosteroid Therapy: Mean AM PEF by Study Week

Patients Previously on Inhaled Corticosteroids

In a 6-week clinical trial, 323 patients, who exhibited a deterioration in asthma control during an inhaled corticosteroid washout period, were randomized to daily treatment with either 40, 160, or 320 mcg twice daily QVAR or 42, 168, or 336 mcg twice daily CFC-BDP. Treatment with increasing doses of both QVAR and CFC-BDP resulted in increased improvement in FEV1, FEF25-75% (forced expiratory flow over 25-75% of the vital capacity), and asthma symptoms. Shown below is the change from baseline in FEV1 as percent predicted after 6 weeks of treatment.

A 6-Week Dose Response Clinical Trial in Patients with Inhaled Corticosteroid Dependent Asthma:
Mean Change in FEV1 as Percent of Predicted

Patients Previously Maintained on Oral Corticosteroids

Clinical experience has shown that some patients with asthma who require oral corticosteroid therapy for control of symptoms can be partially or completely withdrawn from oral corticosteroids if therapy with beclomethasone dipropionate aerosol is substituted. Inhaled corticosteroids may not be effective for all patients with asthma or at all stages of the disease in a given patient.

Pediatric Experience

In one 12-week clinical trial, pediatric patients (age 5-12 years) with symptomatic asthma (N=353) being treated with as-needed beta-agonist bronchodilators were randomized to receive either 40 mcg or 80 mcg twice daily of HFA beclomethasone dipropionate or placebo. Both doses were effective in improving asthma control with significantly greater improvements in FEV1 (9% and 10% predicted change from baseline at week 12 in FEV1 percent predicted, respectively) than with placebo (4% predicted change).

INDICATIONS AND USAGE

QVAR is indicated in the maintenance treatment of asthma as prophylactic therapy in patients 5 years of age and older. QVAR is also indicated for asthma patients who require systemic corticosteroid administration, where adding QVAR may reduce or eliminate the need for the systemic corticosteroids.

Beclomethasone dipropionate is NOT indicated for the relief of acute bronchospasm.

CONTRAINDICATIONS

QVAR is contraindicated in the primary treatment of status asthmaticus or other acute episodes of asthma where intensive measures are required. Hypersensitivity to any of the ingredients of this preparation contraindicates its use.

WARNINGS

Particular care is needed in patients who are transferred from systemically active corticosteroids to QVAR because deaths due to adrenal insufficiency have occurred in asthmatic patients during and after transfer from systemic corticosteroids to less systemically available inhaled corticosteroids. After withdrawal from systemic corticosteroids, a number of months are required for recovery of hypothalamic-pituitary-adrenal (HPA) function.

Patients who have been previously maintained on 20 mg or more per day of prednisone (or its equivalent) may be most susceptible, particularly when their systemic corticosteroids have been almost completely withdrawn. During this period of HPA suppression, patients may exhibit signs and symptoms of adrenal insufficiency when exposed to trauma, surgery, or infections (particularly gastroenteritis) or other conditions with severe electrolyte loss. Although QVAR may provide control of asthmatic symptoms during these episodes, in recommended doses it supplies less than normal physiological amounts of glucocorticoid systemically and does NOT provide the mineralocorticoid that is necessary for coping with these emergencies.

During periods of stress or a severe asthmatic attack, patients who have been withdrawn from systemic corticosteroids should be instructed to resume oral corticosteroids (in large doses) immediately and to contact their physician for further instruction. These patients should also be instructed to carry a warning card indicating that they may need supplementary systemic steroids during periods of stress or a severe asthma attack.

Transfer of patients from systemic steroid therapy to QVAR may unmask allergic conditions previously suppressed by the systemic steroid therapy, e.g., rhinitis, conjunctivitis, and eczema.

Persons who are on drugs which suppress the immune system are more susceptible to infections than healthy individuals. Chickenpox and measles, for example, can have a more serious or even fatal course in non-immune children or adults on corticosteroids. In such children or adults who have not had these diseases or been properly immunized, particular care should be taken to avoid exposure. It is not known how the dose, route and duration of corticosteroid administration affects the risk of developing a disseminated infection. Nor is the contribution of the underlying disease and/or prior corticosteroid treatment known. If exposed to chickenpox, prophylaxis with varicella-zoster immune globulin (VZIG) may be indicated. If exposed to measles, prophylaxis with pooled intramuscular immunoglobulin (IG) may be indicated. (See the respective package inserts for complete VZIG and IG prescribing information.) If chickenpox develops, treatment with antiviral agents may be considered.

QVAR is not a bronchodilator and is not indicated for rapid relief of bronchospasm.

As with other inhaled asthma medications, bronchospasm, with an immediate increase in wheezing, may occur after dosing. If bronchospasm occurs following dosing with QVAR, it should be treated immediately with a short acting inhaled bronchodilator. Treatment with QVAR should be discontinued and alternate therapy instituted. Patients should be instructed to contact their physician immediately when episodes of asthma, which are not responsive to bronchodilators, occur during the course of treatment with QVAR. During such episodes, patients may require therapy with oral corticosteroids.

PRECAUTIONS

General

During withdrawal from oral corticosteroids, some patients may experience symptoms of systemically active corticosteroid withdrawal, e.g., joint and/or muscular pain, lassitude and depression, despite maintenance or even improvement of respiratory function. Although suppression of HPA function below the clinical normal range did not occur with doses of QVAR up to and including 640 mcg/day, a dose dependent reduction of adrenal cortisol production was observed. Since inhaled beclomethasone dipropionate is absorbed into the circulation and can be systemically active, HPA axis suppression by QVAR could occur when recommended doses are exceeded or in particularly sensitive individuals. Since individual sensitivity to effects on cortisol production exist, physicians should consider this information when prescribing QVAR. Because of the possibility of systemic absorption of inhaled corticosteroids, patients treated with these drugs should be observed carefully for any evidence of systemic corticosteroid effect. Particular care should be taken in observing patients postoperatively or during periods of stress for evidence of inadequate adrenal response.

It is possible that systemic corticosteroid effects, such as hypercorticism and adrenal suppression, may appear in a small number of patients, particularly at higher doses. If such changes occur, QVAR should be reduced slowly, consistent with accepted procedures for management of asthma symptoms and for tapering of systemic steroids.

A 12 month randomized controlled clinical trial evaluated the effects of HFA beclomethasone dipropionate without spacer versus CFC beclomethasone dipropionate with large volume spacer on growth in children age 5-11. A total of 520 patients were enrolled, of whom 394 received HFA-BDP (100 – 400 mcg/day ex-valve) and 126 received CFC-BDP (200 – 800 mcg/day ex-valve). Similar control of asthma was noted in each treatment arm. When comparing results at month 12 to baseline, the mean growth velocity in children treated with HFA-BDP was approximately 0.5 cm/year less than that noted with children treated with CFC-BDP via large volume spacer.

A reduction in growth velocity in growing children may occur as a result of inadequate control of chronic diseases such as asthma or from use of corticosteroids for treatment. Physicians should closely follow the growth of all pediatric patients taking corticosteroids by any route and weigh the benefits of corticosteroid therapy and asthma control against the possibility of growth suppression.

The long-term and systemic effects of QVAR in humans are still not fully known. In particular, the effects resulting from chronic use of the agent on developmental or immunologic processes in the mouth, pharynx, trachea, and lung are unknown.

Inhaled corticosteroids should be used with caution, if at all, in patients with active or quiescent tuberculosis infection of the respiratory tract; untreated systemic fungal, bacterial, parasitic or viral infections; or ocular herpes simplex.

Rare instances of glaucoma, increased intraocular pressure, and cataracts have been reported following the inhaled administration of corticosteroids.

Information for Patients

Patients being treated with QVAR should receive the following information and instructions. This information is intended to aid them in the safe and effective use of this medication. It is not a disclosure of all possible adverse or intended effects.

Persons who are on immunosuppressant doses of corticosteroids should be warned to avoid exposure to chickenpox or measles. Patients should also be advised that if they are exposed to these diseases, medical advice should be sought without delay.

Patients should use QVAR at regular intervals as directed. Results of clinical trials indicated significant improvements may occur within the first 24 hours of treatment in some patients; however, the full benefit may not be achieved until treatment has been administered for 1 to 2 weeks, or longer. The patient should not increase the prescribed dosage but should contact their physician if symptoms do not improve or if the condition worsens.

Patients should be advised that QVAR is not intended for use in the treatment of acute asthma. The patient should be instructed to contact their physician immediately if there is any deterioration of their asthma.

Patients should be instructed on the proper use of their inhaler. Patients may wish to rinse their mouth after QVAR use. The patient should also be advised that QVAR may have a different taste and inhalation sensation than that of an inhaler containing CFC propellant.

QVAR use should not be stopped abruptly. The patient should contact their physician immediately if use of QVAR is discontinued.

For the proper use of QVAR, the patient should read and carefully follow the accompanying Patient's Instructions.

Carcinogenesis, Mutagenesis, Impairment of Fertility

The carcinogenicity of beclomethasone dipropionate was evaluated in rats which were exposed for a total of 95 weeks, 13 weeks at inhalation doses up to 0.4 mg/kg/day and the remaining 82 weeks at combined oral and inhalation doses up to 2.4 mg/kg/day. There was no evidence of carcinogenicity in this study at the highest dose, which is approximately 30 and 55 times the maximum recommended daily inhalation dose in adults and children, respectively, on a mg/m^2 basis.

Beclomethasone dipropionate did not induce gene mutation in the bacterial cells or mammalian Chinese Hamster ovary (CHO) cells in vitro. No significant clastogenic effect was seen in cultured CHO cells in vitro or in the mouse micronucleus test in vivo.

In rats, beclomethasone dipropionate caused decreased conception rates at an oral dose of 16 mg/kg/day (approximately 200 times the maximum recommended daily inhalation dose in adults on a mg/m^2 basis). Impairment of fertility, as evidence by inhibition of the estrous cycle in dogs, was observed following treatment by the oral route at a dose of 0.5 mg/kg/day (approximately 20 times the maximum recommended daily inhalation dose in adults on a mg/m^2 basis). No inhibition of the estrous cycle in dogs was seen following 12 months of exposure to beclomethasone dipropionate by the Inhalation route at an estimated daily dose of 0.33 mg/kg (approximately 15 times the maximum recommended daily inhalation dose in adults on a mg/m^2 basis).

Pregnancy

Teratogenic Effects

Pregnancy Category C

Like other corticosteroids, parenteral (subcutaneous) beclomethasone dipropionate was teratogenic and embryocidal in the mouse and rabbit when given at a dose of 0.1 mg/kg/day in mice or at a dose of 0.025 mg/kg/day in rabbits. These doses in mice and rabbits were approximately one-half the maximum recommended daily inhalation dose in adults on a mg/m^2 basis. No teratogenicity or embryocidal effects were seen in rats when exposed to an inhalation dose of 15 mg/kg/day (approximately 190 times the maximum recommended daily inhalation dose in adults on a mg/m^2 basis). There are no adequate and well controlled studies in pregnant women. Beclomethasone dipropionate should be used during pregnancy only if the potential benefit justifies the potential risk to the fetus.

Non-teratogenic Effects

Findings of drug-related adrenal toxicity in fetuses following administration of beclomethasone dipropionate to rats suggest that infants born of mothers receiving substantial doses of QVAR during pregnancy should be observed for adrenal suppression.

Nursing Mothers

Corticosteroids are secreted in human milk. Because of the potential for serious adverse reactions in nursing infants from QVAR, a decision should be made whether to discontinue nursing or to discontinue the drug, taking into account the importance of the drug to the mother.

Pediatric Use

Eight-hundred and thirty-four children between the ages of 5 and 12 were treated with HFA beclomethasone dipropionate (HFA BDP) in clinical trials. The safety and effectiveness of QVAR in children below 5 years of age have not been established.

Use of QVAR with a spacer device in children less than 5 years of age is not recommended. In vitro dose characterization studies were performed with QVAR 40 mcg/actuation with the Optichamber and AeroChamber Plus® spacer utilizing inspiratory flows representative of children under 5 years old. These studies indicated that the amount of medication delivered through the spacing device decreased rapidly with increasing wait times of 5 to 10 seconds as shown in Table 1. If QVAR is used with a spacer device, it is important to inhale immediately.

Based on the average inspiratory flow rates generated by children 6 months to 5 years old, the projected daily dose derived from QVAR 40 mcg at one puff per day at various wait times is depicted in the table below:

TABLE 1
 | Wait time, seconds | Mean medication delivery through AeroChamber, mcg/actuation [Summary Report; Pediatric Dose Characterization of QVAR with Spacer; 3M Pharmaceutical Development, July 21, 2004.] | Body Weight 50th percentile, kg [CDC Growth charts, developed by the National Center for Health Statistics in collaboration with the National Center for Chronic Disease Prevention and Health Promotion (2000).] | Medication delivered per dose, mcg/kg [Includes an estimated 20% loss in the masks] , [QVAR 40mcg in an average adult without using a spacer delivers approximately 0.4 mcg/kg, or bid, 0.8 mcg/kg/day.]
Age 6 months, Flow rate 4.8 L/min | 0 | 11.5 | 7.6 | 1.2
Age 2 years, Flow rate 8.2 L/min | 0 | 14.1 | 13.5 | 0.83
Age 2 years, Flow rate 8.2 L/min | 5 | 5.4 | 13.5 | 0.32
Age 2 years, Flow rate 8.2 L/min | 10 | 3.9 | 13.5 | 0.23
Age 5 years, Flow rate 11.0 L/min | 0 | 17.5 | 18 | 0.78

Oral inhaled corticosteroids have been shown to cause a reduction in growth velocity in children and teenagers with extended use. If a child or teenager on any corticosteroid appears to have growth suppression, the possibility that they are particularly sensitive to this effect of corticosteroids should be considered (see PRECAUTIONS, General).

Geriatric Use

Clinical studies of QVAR did not include sufficient numbers of subjects aged 65 and over to determine whether they respond differently from younger subjects. Other reported clinical experience has not identified differences in responses between the elderly and younger patients. In general, dose selection for an elderly patient should be cautious, usually starting at the low end of the dosing range, reflecting the greater frequency of decreased hepatic, renal, or cardiac function, and of concomitant disease or other drug therapy.

ADVERSE REACTIONS

The following reporting rates of common adverse experiences are based upon four clinical trials in which 1196 Patients (671 female and 525 male adults previously treated with as-needed bronchodilators and/or inhaled corticosteroids) were treated with QVAR (doses of 40, 80, 160, or 320 mcg twice daily) or CFC-BDP (doses of 42, 168, or 336 mcg twice daily) or placebo. The table below includes all events reported by patients taking QVAR (whether considered drug related or not) that occurred at a rate over 3% for either QVAR or CFC-BDP. In considering these data, difference in average duration of exposure and clinical trial design should be taken into account.

Adverse Events Reported by at Least 3% of the Patients for Either QVAR or CFC-BDP by Treatment and Daily Dose
Adverse Events |  | QVAR |  |  |  | CFC-BDP
Adverse Events | Placebo (N=289) % | Total (N=624) % | 80-160 mcg (N=233) % | 320 mcg (N=335) % | 640 mcg (N=56) % | Total (N=283) % | 84 mcg (N=59) % | 336 mcg (N=55) % | 672 mcg (N=169) %
HEADACHE | 9 | 12 | 15 | 8 | 25 | 15 | 14 | 11 | 17
PHARYNGITIS | 4 | 8 | 6 | 5 | 27 | 10 | 12 | 9 | 10
UPPER RESP TRACT INFECTION | 11 | 9 | 7 | 11 | 5 | 12 | 3 | 9 | 17
RHINITIS | 9 | 6 | 8 | 3 | 7 | 11 | 15 | 9 | 10
INCREASED ASTHMA SYMPTOMS | 18 | 3 | 2 | 4 | 0 | 8 | 14 | 5 | 7
ORAL SYMPTOMS INHALATION ROUTE | 2 | 3 | 3 | 3 | 2 | 6 | 7 | 5 | 5
SINUSITIS | 2 | 3 | 3 | 3 | 0 | 4 | 7 | 2 | 4
PAIN | <1 | 2 | 1 | 2 | 5 | 3 | 3 | 5 | 2
BACK PAIN | 1 | 1 | 2 | <1 | 4 | 4 | 2 | 4 | 4
NAUSEA | 0 | 1 | <1 | 1 | 2 | 3 | 5 | 5 | 1
DYSPHONIA | 2 | <1 | 1 | 0 | 4 | 4 | 0 | 0 | 6

Other adverse events that occurred in these clinical trials using QVAR with an incidence of 1% to 3% and which occurred at a greater incidence than placebo were: dysphonia, dysmenorrhea and coughing.

No patients treated with QVAR in the clinical development program developed symptomatic oropharyngeal candidiasis.

If such an infection develops, treatment with appropriate antifungal therapy or discontinuance of treatment with QVAR may be required.

Pediatric Studies

In two 12-week placebo controlled studies in steroid naive pediatric patients 5 to 12 years of age, no clinically relevant differences were found in the pattern, severity, or frequency of adverse events compared with those reported in adults, with the exception of conditions which are more prevalent in a pediatric population generally.

Adverse Event Reports from Other Sources

Rare cases of immediate and delayed hypersensitivity reactions, including urticaria, angioedema, rash, and bronchospasm, have been reported following the oral and intranasal inhalation of beclomethasone dipropionate.

OVERDOSAGE

There were no deaths over 15 days following the oral administration of a single dose of 3000 mg/kg in mice, 2000 mg/kg in rats, and 1000 mg/kg in rabbits. The doses in mice, rats, and rabbits were 19,000, 25,000, and 25,000 times, respectively, the maximum recommended daily inhalation in adults or 36,000, 48,000, and 48,000 times, respectively the maximum recommended daily inhalation dose in children on a mg/m^2 basis.

DOSAGE AND ADMINISTRATION

Patients should prime QVAR by actuating into the air twice before using for the first time or if QVAR has not been used for over ten days. Avoid spraying in the eyes or face when priming QVAR. QVAR is a solution aerosol, which does not require shaking. Consistent dose delivery is achieved, whether using the 40 or 80 mcg strengths, due to proportionality of the two products (i.e., two actuations of 40 mcg strength should provide a dose comparable to one actuation of the 80 mcg strength).

QVAR should be administered by the oral inhaled route in patients 5 years of age and older. Use of QVAR with a spacer device in children less than 5 years of age is not recommended (see PRECAUTIONS, Pediatric Use). The onset and degree of symptom relief will vary in individual patients. Improvement in asthma symptoms should be expected within the first or second week of starting treatment, but maximum benefit should not be expected until 3-4 weeks of therapy. For patients who do not respond adequately to the starting dose after 3-4 weeks of therapy, higher doses may provide additional asthma control. The safety and efficacy of QVAR when administered in excess of recommended doses has not been established.

Table 2: Recommended Dosing for Adults and Adolescents
Patient's Previous Therapy | Recommended Starting Dose | Highest Recommended Dose
Bronchodilators Alone | 40 to 80 mcg twice daily | 320 mcg twice daily
Inhaled Corticosteroids | 40 to 160 mcg twice daily | 320 mcg twice daily

Table 3: Recommended Dosing for Children 5 to 11 Years
Patient's Previous Therapy | Recommended Starting Dose | Highest Recommended Dose
Bronchodilators Alone | 40 mcg twice daily | 80 mcg twice daily
Inhaled Corticosteroids | 40 mcg twice daily | 80 mcg twice daily

As with any inhaled corticosteroid, physicians are advised to titrate the dose of QVAR downward over time to the lowest level that maintains proper asthma control. This is particularly important in children since a controlled study has shown that QVAR has the potential to affect growth in children. Patients should be instructed on the proper use of their inhaler.

Patients Not Receiving Systemic Corticosteroids

Patients who require maintenance therapy of their asthma may benefit from treatment with QVAR at the doses recommended above. In patients who respond to QVAR, improvement in pulmonary function is usually apparent within 1 to 4 weeks after the start of therapy. Once the desired effect is achieved, consideration should be given to tapering to the lowest effective dose.

Patients Maintained on Systemic Corticosteroids

QVAR may be effective in the management of asthmatics maintained on systemic corticosteroids and may permit replacement or significant reduction in the dosage of systemic corticosteroids.

The patient's asthma should be reasonably stable before treatment with QVAR is started. Initially, QVAR should be used concurrently with the patient's usual maintenance dose of systemic corticosteroids. After approximately one week, gradual withdrawal of the systemic corticosteroids is started by reducing the daily or alternate daily dose. Reductions may be made after an interval of one or two weeks, depending on the response of the patient. A slow rate of withdrawal is strongly recommended. Generally these decrements should not exceed 2.5 mg of prednisone or its equivalent. During withdrawal, some patients may experience symptoms of systemic corticosteroid withdrawal, e.g. joint and/or muscular pain, lassitude and depression, despite maintenance or even improvement in pulmonary function. Such patients should be encouraged to continue with the inhaler but should be monitored for objective signs of adrenal insufficiency. If evidence of adrenal insufficiency occurs, the systemic corticosteroid doses should be increased temporarily and thereafter withdrawal should continue more slowly.

During periods of stress or a severe asthma attack, transfer patients may require supplementary treatment with systemic corticosteroids.

DIRECTIONS FOR USE

Illustrated Patient's Instructions for proper use accompany each package of QVAR.

HOW SUPPLIED

QVAR is supplied in two strengths:

QVAR 40 mcg is supplied either in a 7.3 g canister containing 100 actuations with a beige plastic actuator and gray dust cap, and Patient's Instructions; box of one; 100 Actuations – NDC 59310-175-40 or in an 8.7 g canister containing 120 actuations with a beige plastic actuator and gray dust cap, and Patient's Instructions; box of one; 120 Actuations – NDC 59310-202-40
QVAR 80 mcg is supplied either in a 7.3 g canister containing 100 actuations with a dark mauve plastic actuator and gray dust cap, and Patient's Instructions; box of one; 100 Actuations – NDC 59310-177-80 or in an 8.7 g canister containing 120 actuations with a dark mauve plastic actuator and gray dust cap, and Patient's Instructions; box of one; 120 Actuations – NDC 59310-204-80

The correct amount of medication in each inhalation cannot be assured after 100 actuations from the 7.3 g canister or 120 actuations from the 8.7 g canister even though the canister is not completely empty. The canister should be discarded when the labeled number of actuations have been used.

STORAGE AND HANDLING

Store QVAR Inhalation Aerosol when not being used, so that the product rests on the concave end of the canister with the plastic actuator on top.

Store at 25°C (77°F).

Excursions between 15° and 30°C (59° and 86°F) are permitted (see USP). For optimal results, the canister should be at room temperature when used. QVAR Inhalation Aerosol canister should only be used with the QVAR Inhalation Aerosol actuator and the actuator should not be used with any other inhalation drug product.

CONTENTS UNDER PRESSURE

Do not puncture. Do not use or store near heat or open flame. Exposure to temperatures above 49°C (120°F) may cause bursting. Never throw container into fire or incinerator.

Keep out of reach of children.

Rx only

U.S. Patent Nos. 5605674, 5683677, 5695743, 5776432

Mktd by:
Teva Respiratory, LLC– Horsham, PA 19044

Developed and Manufactured by: 3M Drug Delivery Systems Northridge, CA 91324 | OR | 3M Health Care, Ltd. Loughborough, UK

September, 2010
© 2010 Teva Respiratory, LLC
639300
QVAR® is a registered trademark of IVAX LLC, a member of the TEVA Group.
Rev. 09/10

OptiChamber is a registered trademark of Respironics Healthscan, Inc. and AeroChamber Plus is a registered trademark of Trudell Medical International Trudell Partnership Holdings Limited and Packard Medical Supply Centre Ltd.

PATIENT'S INSTRUCTIONS

QVAR®
(beclomethasone dipropionate HFA)
INHALATION AEROSOL

Attention Pharmacist: Detach "PATIENT'S INSTRUCTIONS for Use" from package insert and dispense with the product.

PATIENT'S INSTRUCTIONS

It is important that you read these instructions before using QVAR.

Correct and regular use of the inhaler will prevent or lessen the severity of asthma attacks.

1. Remove the plastic cap (see Figure 1) and be sure there are no foreign objects in the mouthpiece.

Figure 1

2. As with all aerosol medications, it is recommended to prime the QVAR inhaler before using for the very first time after purchase, and in cases where the inhaler has not been used for more than ten days. Prime by releasing two actuations into the air, away from your eyes and face. Be sure the canister is firmly seated in the plastic mouthpiece adapter before each use.

3. BREATHE OUT AS FULLY AS YOU COMFORTABLY CAN. Hold the inhaler as shown in Figure 2. Close your lips around the mouthpiece, keeping your tongue below it.

Figure 2

4. WHILE BREATHING IN DEEPLY AND SLOWLY, PRESS DOWN ON THE CAN WITH YOUR FINGER. When you have finished breathing in, hold your breath as long as you comfortably can (i.e., 5 - 10 seconds).

5. TAKE YOUR FINGER OFF THE CAN and remove the inhaler from your mouth. Breathe out gently.

6. If your physician has told you to take more than one inhalation per treatment repeat steps 3 through 5.

7. You should rinse your mouth with water after treatment.

8. For normal hygiene, the mouthpiece of your inhaler should be cleaned weekly with a clean, dry tissue or cloth.

DO NOT WASH OR PUT ANY PART OF YOUR INHALER IN WATER.

9. DISCARD THE CANISTER AFTER the date calculated by your physician or pharmacist. The correct amount of medication in each inhalation cannot be assured after 100 actuations from the 7.3 g canister or 120 actuations from the 8.7 g canister even though the canister is not completely empty. The canister should be discarded when the labeled number of actuations have been used. Before the discard date you should consult your physician to determine whether a refill is needed. It is advisable to keep track of the number of doses taken from the canister to better predict when a refill is necessary. Just as you should not take extra doses without consulting your physician, you also should not stop taking QVAR without consulting your physician.

IMPORTANT QVAR is preventive therapy for asthma and must be used regularly and at the times your physician has prescribed.

DO NOT CONFUSE QVAR WITH OTHER ASTHMA MEDICATION. QVAR WILL NOT PROVIDE IMMEDIATE RELIEF IF YOU ARE HAVING AN ASTHMA ATTACK.

Your physician will decide whether other medication is needed should you require immediate relief. If you also use another medicine by inhalation, you should consult your physician for instructions on when to use it in relation to using QVAR. If this is the first time you will be using QVAR, it may take from 1 to 4 weeks before you feel the full benefits.

QVAR Inhalation Aerosol canister should only be used with the QVAR Inhalation Aerosol mouthpiece and the mouthpiece should not be used with any other inhalation drug product.

DOSAGE

Use only as directed by your physician.

CONTENTS UNDER PRESSURE

Do not puncture. Do not use or store near heat or open flame. Exposure to temperatures above 49°C (120°F) may cause bursting. Never throw container into fire or incinerator.

Keep out of reach of children.

Avoid spraying in eyes.

Store at 25°C (77°F). For optimal results, the canister should be at room temperature when used. Store QVAR Inhalation Aerosol when not being used, so that the product rests on the concave end of the canister with the plastic actuator on top.

Mktd by:
Teva Respiratory, LLC
Horsham, PA 19044

Developed and Manufactured by: 3M Drug Delivery Systems Northridge, CA 91324 | OR | 3M Health Care, Ltd. Loughborough, UK

© 2010 Teva Respiratory, LLC
QVAR® is a registered trademark of IVAX LLC, a member of the TEVA Group.

639300
Rev. 09/10